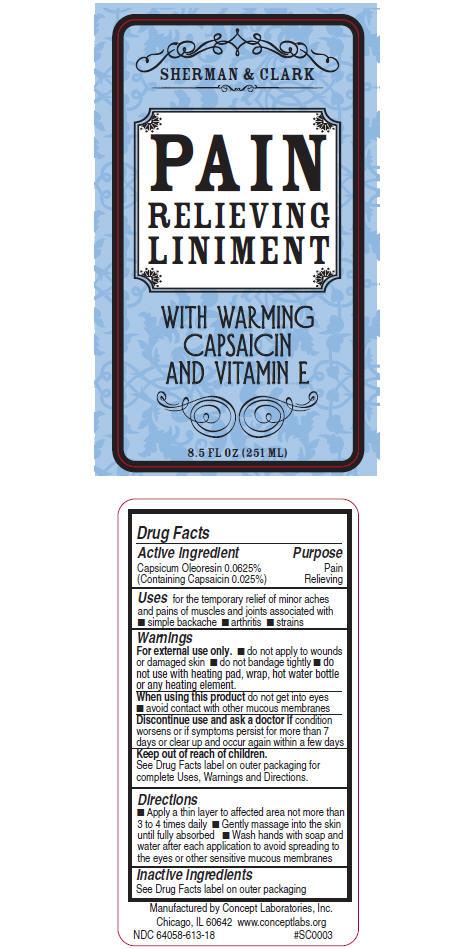 DRUG LABEL: Sherman and Clark Pain Relieving
NDC: 64058-613 | Form: GEL
Manufacturer: Concept Laboratories, Inc.
Category: otc | Type: HUMAN OTC DRUG LABEL
Date: 20111020

ACTIVE INGREDIENTS: Capsaicin 0.06275 g/251 mL
INACTIVE INGREDIENTS: Water; Glycerin; PEG-75 LANOLIN; DIMETHYL SULFONE; ALOE VERA LEAF; MEDICAGO SATIVA LEAF; CYMBOPOGON SCHOENANTHUS LEAF; GLUCOSAMINE HYDROCHLORIDE; GINKGO; POLYSORBATE 20; EMU OIL; DMDM HYDANTOIN; PROPYLENE GLYCOL; METHYLPARABEN; PROPYLPARABEN

SHERMAN & CLARK PAIN RELIEVING LINIMENT

Drug Facts

Active ingredient

Capsicum Oleoresin 0.0625%
(Containing Capsaicin 0.025%)

Purpose

Pain Relieving

Uses

for the temporary relief of minor aches and pains of muscles and joints associated with n simple backache n arthritis n strains n sprains n bruises

Warnings

For external use only.

DO NOT USE

Do not apply to wounds or damaged skin. Do not bandage tightly. Do not use with heating pad, wrap, hot water bottle or any heating element.

When using this product do not get into eyes. Avoid contact with other mucous membranes

STOP USE

Discontinue use and ask a doctor if condition worsens or if symptoms persist for more than 7 days or clear up and occur again within a few days

Keep out of reach of children.

If swallowed, get medical help or contact a Poison Control center right away. If pregnant or nursing, seek the advice of a health professional before using

Directions

Children under 12 years of age consult a physician

Apply a thin layer to affected area not more than 3 to 4 times daily

Gently massage into the skin until fully absorbed

Wash hands with soap and water after each application to avoid spreading to the eyes or other sensitive mucous membranes

Other information

It is recommended to test for skin sensitivity prior to use. Apply product to a small area, follow the directions and wait 24 hours. Proceed with application if no adverse reaction. A burning sensation may occur upon initial application but generally disappears with continued use. For a severe burning discomfort, remove excess product with a soft cloth and cooking oil. If applying product to hands, wait 30 minutes before washing.

Avoid water, heat, or direct sunlight while using product. If wearing contact lenses, insert prior to application and avoid touching them after applying product. If eye contact occurs, flush immediately with water.

Inactive ingredients

Water (Aqua), Glycerin, PEG-75 Lanolin, Aloe Barbadensis Leaf Juice, PEG-40 Hydrogenated Castor Oil, Acrylates/C10-30 Alkyl Acrylate Crosspolymer, Triethanolamine, Polysorbate 20, Glucosamine HCl, Emu Oil, Dimethyl Sulfone, Celosia Argentea Seed Extract, Ginkgo Biloba Extract, Panax Ginseng Root Extract, Medicago Sativa (Alfalfa) Extract, Cymbopogon Schoenanthus Extract, Tocopheryl Acetate, DMDM Hydantoin, Propylene Glycol, Methylparaben, Propylparaben.

Questions or comments?

Call 1-888-373-8831 or visit www.conceptlabs.org

Manufactured by Concept Laboratories, Inc., Chicago, IL 60642
#BG-#SC0003

PRINCIPAL DISPLAY PANEL - 251 ML Bottle Label

Sherman & Clark

PAIN
RELIEVING
LINIMENT

WITH WARMING
CAPSAICIN
AND VITAMIN E

8.5 FL OZ (251 ML)